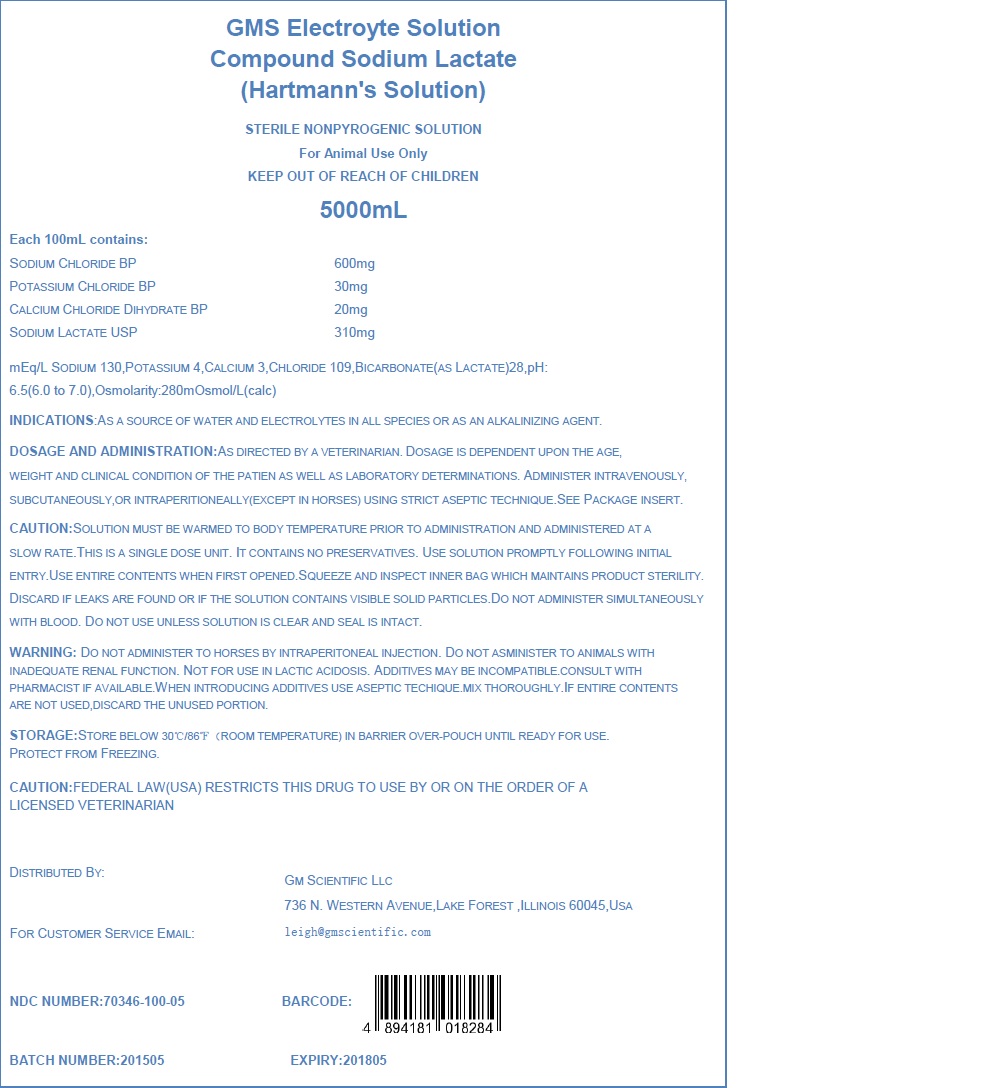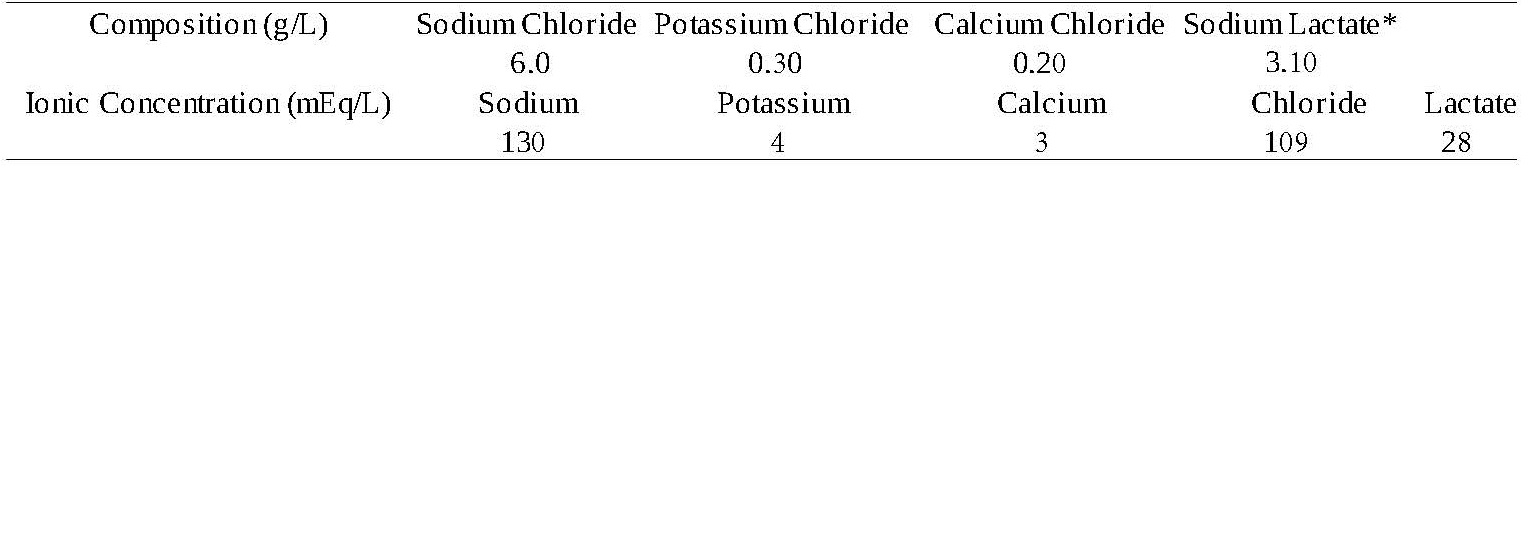 DRUG LABEL: GMS Electrolyte Solution Compound Sodium Lactate Hartmanns
NDC: 70346-100 | Form: SOLUTION
Manufacturer: GM Scientific, LLC
Category: animal | Type: PRESCRIPTION ANIMAL DRUG LABEL
Date: 20150622

ACTIVE INGREDIENTS: SODIUM CHLORIDE 600 mg/100 mL; POTASSIUM CHLORIDE 30 mg/100 mL; CALCIUM CHLORIDE 20 mg/100 mL; SODIUM LACTATE 310 mg/100 mL
INACTIVE INGREDIENTS: WATER

GMS Electrolyte Solution Compound Sodium Lactate Hartmanns

Description

GMS Electrolyte Solution Compound Sodium Lactate (Hartmanns Solution) is a sterile, non-pyrogenic solution intended for fluid and electrolyte replenishment in single dose containers. May be administered intravenously, subcutaneously or intraperitoneally (except in horses) using aseptic technique. It contains no antimicrobial agents. Discard any unused portion. Composition, osmolarity, pH and ionic concentration are shown in Table 1.

Table 1

*Sodium Lactate USP (S)-enantiomer

Osmolarity (mOsmol/L) (calc): 280mOsmol per litre

pH: 6.5 (limit 6.0 7.0)

The container is free of PVC and phthalates. It is fabricated from 5 layer polyolefin based co-extrusion material. The container meets the requirements of USP (Class VI).

Clinical Pharmacology

A multiple electrolyte intravenous solution is intended to restore the electrolyte balance and water for hydration. A combination of multiple electrolytes and sodium lactate, an alkalinizing agent, will provide electrolyte balance and normalize the pH of the acid-base of the physiological system.

Indications

GMS Electrolyte Solution Compound Sodium Lactate (Hartmann’s Solution) is indicated as a source of water and electrolytes for all species. It is also used as an alkalinizing agent.

Contraindications

GMS Electrolyte Solution Compound Sodium Lactate (Hartmann’s Solution) is contraindicated in patients with a known hypersensitivity to sodium lactate; congestive heart failure or severe impairment of renal function; clinical states in which the administration of sodium and chloride is detrimental.

Warnings

The introduction of additives to any solution, regardless of type of container, requires special attention to ensure that no incompatibilities result. While some incompatibilities are readily absorbed, one must be aware that subtle physical, chemical and pharmacological incompatibilities can occur. The medical literature, the package insert and other available sources of information should be reviewed for thorough understanding of possible incompatibilities.

GMS Electrolyte Solution Compound Sodium Lactate (Hartmann’s Solution) should be used with great care, if at all, in patients with congestive heart failure, severe renal insufficiency, and in clinical states in which there exists edema and sodium retention.

GMS Electrolyte Solution Compound Sodium Lactate (Hartmann’s Solution) should be used with great care, if at all, in patients with hyperkalemia, severe renal failure, and in conditions in which potassium retention is present.

GMS Electrolyte Solution Compound Sodium Lactate (Hartmann’s Solution) should be used with great care in patients with metabolic or respiratory alkalosis. The administration of lactate ions should be done with great care in those conditions in which there is an increased level or an impaired utilization of these ions, such as severe hepatic insufficiency.

GMS Electrolyte Solution Compound Sodium Lactate (Hartmann’s Solution) should not be administered simultaneously with blood through the same administration set because of likelihood of coagulation.

The intravenous administration of GMS Electrolyte Solution Compound Sodium Lactate (Hartmann’s Solution) can cause fluid and/or solute overloading resulting in dilution of serum electrolyte concentrations, over-hydration, congested states, or pulmonary edema. The risk of dilutional states is inversely proportional to the electrolyte concentrations of the injections. The risk of solute overloading causing congested states with peripheral and pulmonary edema is directly proportional to the electrolyte concentrations of the injections.

In patients with diminished renal function, administration of GMS Electrolyte Solution Compound Sodium Lactate (Hartmann’s Solution) may result in sodium or potassium retention.

Do not administer to horses by intraperitoneal injection. Do not administer to animals with inadequate renal function. Not for use in lactic acidosis.

Adverse Reactions

Adverse reactions may occur due to the solution or the technique of administration including fever response, infection at the site of injection or allergic reactions. Prolonged intravenous infusion of this type of product may cause venous thrombosis or phlebitis extending from the site of injection, extravasation, and hypervolemia.

If an adverse reaction does occur, discontinue the infusion and evaluate the patient, institute appropriate therapeutic countermeasures, and save the remainder of the fluid for examination if deemed necessary.

Precautions

This is a single dose unit. It contains no preservatives. Use entire contents when first opened.

Clinical evaluation and periodic laboratory determinations are necessary to monitor changes in fluid balance, electrolyte concentrations, and acid base balance during prolonged therapy or whenever the condition of the patient warrants such evaluation.

GMS Electrolyte Solution Compound Sodium Lactate (Hartmann’s Solution) should be used with caution. Excess administration may result in metabolic alkalosis.

Do not administer unless solution is clear and both seal and container are intact.

Solution must be warmed to body temperature prior to administration and administered at a slow rate. Use solution promptly following initial entry.

Reactions which may occur because of the solution or the technique of administration, include febrile response, infection at the site of injection, extravasation, and hypervolemia.

If an adverse reaction does occur, discontinue the infusion and evaluate the patient, institute appropriate therapeutic countermeasures, and save the remainder of the fluid for examination if deemed necessary.

Dosage and Administration

To be used as directed by a licensed veterinarian. The dosage of the GMS Electrolyte Solution Compound Sodium Lactate (Hartmann’s Solution) is dependent upon the age, weight and clinical conditions of the patient as well as laboratory determinations. Parenteral drug products should be inspected visually for particulate matter and discoloration prior to administration.

For use in one patient on one occasion only. Discard any unused portion. Care should be taken with administration technique to avoid administration site reactions and infection.

Additives may be incompatible. Complete information is not available. Those additives known to be incompatible should not be used. Consult with Pharmacist, if available. If, in the informed judgement of the doctor, it is deemed advisable to introduce additives, use aseptic technique. Mix thoroughly when additives have been introduced. Do not store solutions containing additives.

Over-dosage

In an event of over-hydration or solute overload, re-evaluate the patient and institute appropriate corrective measures. See Warnings, Precautions and Adverse Events.

Packs Supplied

GMS Electrolyte Solution Compound Sodium Lactate (Hartmann’s Solution) in plastic container is available as follows:

Size (mL) | Item Code | NDC
5000 | EQLRS-5 | 70346-100-05

Exposure of pharmaceutical products to heat should be minimized. Avoid excessive heat. It is recommended the product be stored at room temperature (30°C/86°F). Protect from freezing.

Directions for use of plastic container

To Open

Tear overwrap at slit and remove solution container. Some opacity of the plastic due to moisture absorption during the sterilization process may be observed. This is normal and does not affect the solution quality or safety. The opacity will diminish gradually. Check for minute leaks by squeezing solution container firmly. If leaks are found, discard solution as sterility may be impaired. If supplemental medication is desired, follow directions below:

Preparation for Administration

1. Suspend container from eyelet support.
2. Remove plastic protector from inlet/outlet port at bottom of container.
3. Attach administration set.

To Add Medication

WARNING: Additives may be incompatible.

To add medication before solution administration

1. Prepare medication site.
2. Using syringe with 0.63mm to 0.80mm needle, puncture medication port and inject.
3. Mix solution and medication thoroughly. For high density medication such as potassium chloride, squeeze ports while ports are upright and mix thoroughly.

To add medication during solution administration

1. Close the clamp on the administration set.
2. Prepare medication site.
3. Using syringe with 0.63mm to 0.80mm needle, puncture medication port and inject.
4. Remove container from IV pole and/or turn to an upright position.
5. Evacuate both ports by squeezing them while container is in the upright position.
6. Mix solution and medication thoroughly.
7. Return container to in use position and continue administration.

CAUTION: FEDERAL LAW RESTRICTS THIS DRUG TO USE BY OR ON THE ORDER OF A LICENSED VETERINARIAN.

Distributed by:

GM Scientific LLC.

736 N. Western Avenue, Lake Forest, Illinois 60045, USA

For customer service email:

leigh@gmscientific.com

Version: US_01